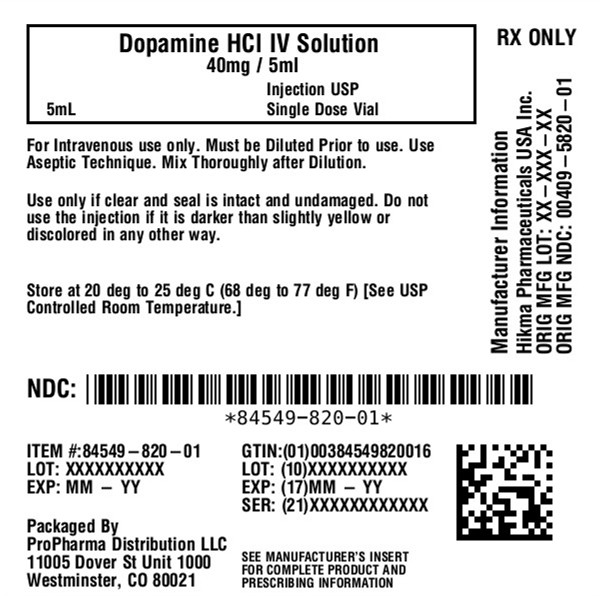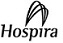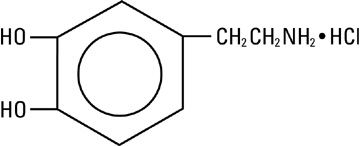 DRUG LABEL: DOPamine Hydrochloride
NDC: 84549-820 | Form: INJECTION, SOLUTION, CONCENTRATE
Manufacturer: ProPharma Distribution
Category: prescription | Type: HUMAN PRESCRIPTION DRUG LABEL
Date: 20251211

ACTIVE INGREDIENTS: DOPAMINE HYDROCHLORIDE 40 mg/1 mL
INACTIVE INGREDIENTS: SODIUM METABISULFITE 9 mg/1 mL; ANHYDROUS CITRIC ACID 10 mg/1 mL; TRISODIUM CITRATE DIHYDRATE 5 mg/1 mL

HIGHLIGHTS OF PRESCRIBING INFORMATION

These highlights do not include all the information needed to use DOPAMINE HYDROCHLORIDE INJECTION safely and effectively. See full prescribing information for DOPAMINE HYDROCHLORIDE INJECTION.
DOPAMINE HYDROCHLORIDE injection, for intravenous use
Initial U.S. Approval: 1974

1 INDICATIONS AND USAGE

Dopamine HCl Injection is a catecholamine indicated to improve hemodynamic status in patients in shock. (1)

2 DOSAGE AND ADMINISTRATION

Correct hypovolemia, acidosis, and hypoxia prior to use. (2.1)

Administer in a large vein with an infusion pump preferably in an intensive care setting. (2.1)

Recommended starting dosage in adults and pediatric patients is 2 to 5 mcg/kg/minute as a continuous intravenous infusion. Titrate in 5 to 10 mcg/kg/minute increments based on hemodynamic response and tolerability, up to not more than 50 mcg/kg/minute. (2.2)

See the Full Prescribing Information for important preparation instructions and drug incompatibilities. (2.1,2.3)

3 DOSAGE FORMS AND STRENGTHS

The following strengths of Dopamine HCL, USP, are supplied in single-dose vials: (3)

- 200 mg/5 mL (40 mg/mL)
- 400 mg/10 mL (40 mg/mL)

4 CONTRAINDICATIONS

Dopamine is contraindicated in patients with pheochromocytoma. (4)

5 WARNINGS AND PRECAUTIONS

- Tissue ischemia: Severe peripheral and visceral vasoconstriction can occur. Address hypovolemia prior to use, monitor extremities, and infuse into large vein. (5.1)
- Cardiac arrhythmias: Monitor closely. (5.2)
- Hypotension after abrupt discontinuation: Gradually reduce infusion rate while expanding blood volume with intravenous fluids. (5.3)
- Severe hypersensitivity reactions due to sodium metabisulfite excipient: May cause anaphylaxis including life‑threatening or less severe asthmatic episodes in susceptible individuals. (5.4)

6 ADVERSE REACTIONS

The most common adverse reaction is localized vasoconstriction due to extravasation. (6)

To report SUSPECTED ADVERSE REACTIONS, contact Pfizer Inc. at 1-800-438-1985 or FDA at 1-800-FDA-1088 or www.fda.gov/medwatch.

7 DRUG INTERACTIONS

- Halogenated anesthetics: Can sensitize the myocardium to the effects of dopamine and can produce ventricular arrhythmias and hypertension. (7)
- MAO inhibitors: Risk of severe hypertension. Reduce recommended Dopamine HCl Injection dosage. (7)
- Tricyclic antidepressants: Risk of hypertension. Monitor blood pressure. (7)
- Vasopressors: Risk of severe hypertension. Monitor blood pressure. (7)

FULL PRESCRIBING INFORMATION

1 INDICATIONS AND USAGE

Dopamine HCl Injection is indicated to improve hemodynamic status in patients in distributive shock or shock due to reduced cardiac output.

2 DOSAGE AND ADMINISTRATION

2.1 Preparation and Administration Instructions

Correct Hypovolemia, Acidosis, and Hypoxia

Address hypovolemia, acidosis, and hypoxia before initiating Dopamine HCl Injection. If patient does not respond to therapy, suspect occult hypovolemia. Acidosis may reduce the effectiveness of dopamine [see Warnings and Precautions (5.1)] .

Preparation

For the 40‑mg/mL preparation, transfer by aseptic technique the contents containing either 5 mL (200 mg) or 10 mL (400 mg) of Dopamine HCl Injection to either a 250‑mL or a 500‑mL bottle of one of the sterile intravenous solutions listed below:

- 0.9% Sodium Chloride Injection, USP
- 5% Dextrose Injection, USP
- 5% Dextrose and 0.9% Sodium Chloride Injection, USP
- 5% Dextrose and 0.45% Sodium Chloride Injection, USP
- 5% Dextrose and Lactated Ringer’s Injection
- Sodium Lactate Injection, USP 1/6 Molar
- Lactated Ringer’s Injection, USP

The resultant dilutions are summarized in the following chart:

Volume of IV solution | Volume of Dopamine Hydrochloride Injection
Volume of IV solution | 5 mL | 10 mL
250 mL | 800 mcg/mL | 1600 mcg/mL
500 mL | 400 mcg/mL | 800 mcg/mL
1000 mL | 200 mcg/mL | 400 mcg/mL

Dopamine HCl Injection has been found to be stable for 24 hours after dilution in the foregoing intravenous solutions.

Administration

Dopamine HCl Injection is administered (only after dilution) by intravenous infusion.

Administer Dopamine HCl Injection into a large vein [see Warnings and Precautions (5.1)] with the use of an infusion pump preferably in an intensive care setting.

Inspect Dopamine HCl Injection for particulate matter and discoloration prior to administration whenever solution and container permit (the solution is clear, practically colorless). Do not administer if the solution is darker or discolored.

Use higher concentration solutions (e.g., 3200 mcg/mL or 1600 mcg/mL strengths) in patients requiring fluid restriction.

Discontinuation

When discontinuing Dopamine HCl Injection, gradually reduce the infusion rate while expanding blood volume with intravenous fluids [see Warnings and Precautions (5.3)] .

2.2 Recommended Dosage

The recommended starting dosage in adults and pediatric patients is 2 to 5 mcg/kg/minute as a continuous intravenous infusion [see Dosage and Administration (2.3)] . Titrate the infusion rate in increments of 5 to 10 mcg/kg/minute based on hemodynamic response and tolerability, but do not exceed 50 mcg/kg/minute.

Infusion rates may be calculated using the following formula:

Infusion Rate (mL/hour) = [Dose (mcg/kg/minute) x Weight (kg) x 60 (minutes/hour)]

Concentration (mcg/mL)

Example calculations for infusion rates are as follows:

Example 1:for a 60 kg person at the recommended initial dose of 2 mcg/kg/minute using a 800 mcg/mL concentration, the infusion rate would be as follows:

Infusion Rate(mL/hour) = [2 (mcg/kg/minute) x 60 (kg) x 60 (minutes/hour) ] = 9 (mL/hour)

1. 800 (mcg/mL)

Example 2:for a 70 kg person at a dose of 5 mcg/kg/minute using a 1600 mcg/mL concentration, the infusion rate would be as follows:

Infusion Rate(mL/hour) = [5 (mcg/kg/minute) x 70 (kg) x 60 (minutes/hour) ] = 13.13 (mL/hour)

1. 1600 (mcg/mL)

2.3 Drug Incompatibilities

Dopamine HCl Injection is incompatible with the following products; therefore, avoid simultaneous administration (through the same infusion set):

- Sodium bicarbonate or other alkalinizing substances, because dopamine is inactivated in alkaline solution
- Blood, because of the risk of pseudoagglutination of red cells
- Iron salts

Do not add additional medications in the diluted infusion solution.

3 DOSAGE FORMS AND STRENGTHS

The following strengths of Dopamine HCL, USP, are supplied in single-dose vials (the solution is clear practically colorless):

- 200 mg/5 mL (40 mg/mL)
- 400 mg/10 mL (40 mg/mL)

4 CONTRAINDICATIONS

Dopamine is contraindicated in patients with pheochromocytoma.

5 WARNINGS AND PRECAUTIONS

5.1 Tissue Ischemia

Administration of dopamine to patients who are hypotensive from hypovolemia can result in severe peripheral and visceral vasoconstriction, decreased renal perfusion and hypouresis, tissue hypoxia, lactic acidosis, and poor systemic blood flow despite “normal” blood pressure. Address hypovolemia prior to initiating Dopamine HCl Injection [see Dosage and Administration (2.2)] .

Gangrene of the extremities has occurred in patients with occlusive vascular disease or who received prolonged or high dose infusions. Monitor for changes to the skin of the extremities in susceptible patients.

Extravasation of Dopamine HCl Injection may cause necrosis and sloughing of surrounding tissue. To reduce the risk of extravasation, infuse into a large vein [see Dosage and Administration (2.1)] , check the infusion site frequently for free flow, and monitor for signs of extravasation.

Emergency Treatment of Extravasation

To prevent sloughing and necrosis in areas in which extravasation has occurred, infiltrate the ischemic area as soon as possible, using a syringe with a fine hypodermic needle with:

- 5 to 10 mg of phentolamine mesylate in 10 to 15 mL of 0.9% Sodium Chloride Injection in adults
- 0.1 to 0.2 mg/kg of phentolamine mesylate up to a maximum of 10 mg per dose in pediatric patients.

Sympathetic blockade with phentolamine causes immediate and conspicuous local hyperemic changes if the area is infiltrated within 12 hours.

5.2 Cardiac Arrhythmias

Dopamine may cause arrhythmias. Monitor patients with arrhythmias and treat appropriately.

5.3 Hypotension after Abrupt Discontinuation

Sudden cessation of the infusion may result in marked hypotension. Gradually reduce the infusion rate while expanding blood volume with intravenous fluids.

5.4 Severe Hypersensitivity Reactions due to Sodium Metabisulfite Excipient

Dopamine HCl Injection contains sodium metabisulfite, a sulfite that may cause allergic-type reactions including anaphylactic symptoms and life-threatening or less severe asthmatic episodes in certain susceptible people. The overall prevalence of sulfite sensitivity in the general population is unknown and probably low. Sulfite sensitivity is seen more frequently in asthmatic than in nonasthmatic people.

6 ADVERSE REACTIONS

The following adverse reactions are described elsewhere in the labeling:

- Tissue Ischemia [see Warnings and Precautions (5.1)]
- Cardiac Arrhythmias [see Warnings and Precautions (5.2)]
- Hypotension [see Warnings and Precautions (5.3)]
- Severe Hypersensitivity Reactions [see Warnings and Precautions (5.4)]

The following adverse reactions have been identified during postapproval use of dopamine. Because these reactions are reported voluntarily from a population of uncertain size, it is not always possible to reliably estimate their frequency or establish a causal relationship to drug exposure.

Cardiac Disorders:anginal pain, palpitation

Gastrointestinal Disorders:nausea, vomiting

Metabolism and Nutrition Disorders:azotemia

Nervous System Disorders:headache, anxiety

Respiratory Disorders:dyspnea

Skin and Subcutaneous Tissue Disorders:piloerection

Vascular Disorders:hypertension

7 DRUG INTERACTIONS

1. See Table 1 for clinically significant drug interactions with dopamine.

Table 1: Clinically Significant Drug Interactions with Dopamine
Halogenated Anesthetics
Clinical Impact: | Concomitant use may increase cardiac autonomic irritability and can sensitize the myocardium to the action of dopamine which may lead to ventricular arrhythmias and hypertension.
Intervention: | Monitor cardiac rhythm.
Examples: | desflurane, enflurane, isoflurane, and sevoflurane.
MAO Inhibitors
Clinical Impact: | Because dopamine is metabolized by monoamine oxidase (MAO), inhibition of this enzyme prolongs and potentiates the effect of dopamine which may result in severe hypertension and cardiac arrhythmia.
Intervention: | Reduce the recommended starting dosage to no greater than one‑tenth (1/10) of the recommended dose in patients who have been treated with MAO inhibitors within two to three weeks prior to the administration of Dopamine HCl Injection.
Examples: | isocarboxazid, phenelzine, tranylcypromine, rasagiline, selegiline, linezolid.
Tricyclic Antidepressants
Clinical Impact: | Concomitant use may potentiate the cardiovascular effects of dopamine (e.g., hypertension).
Intervention: | Monitor blood pressure.
Examples: | amitriptyline, desipramine, doxepin, imipramine, nortriptyline.
1. Vasopressors
Clinical Impact: | Concomitant use may result in severe hypertension.
Intervention: | Monitor blood pressure.
Examples: | norepinephrine, epinephrine, oxytocin.

8 USE IN SPECIFIC POPULATIONS

8.1 Pregnancy

Risk Summary

There are no human data with dopamine use in pregnant women. There are risks to the mother and fetus from hypotension associated with shock, which can be fatal if left untreated (see Clinical Considerations). In animal reproduction studies, adverse developmental outcomes were observed with intravenous dopamine HCl administration in pregnant rats during organogenesis at doses, on a mcg/m^2basis, of one‑third the human starting dose of 2 mcg/kg/minute (90 mcg/m^2/minute).

The background risk of major birth defects and miscarriage for the indicated population is unknown. All pregnancies carry some risk of birth defect, loss, or other adverse outcomes. In the U.S. general population, the background risk of major birth defects and miscarriage in clinically recognized pregnancies is 2‑4% and 15‑20%, respectively.

Clinical Considerations

Disease-Associated Maternal and/or Embryo/Fetal risk

Hypotension associated with distributive shock, or shock due to reduced cardiac output are medical emergencies in pregnancy which can be fatal if left untreated. Delaying treatment in pregnant women with hypotension associated with distributive shock, or shock due to reduced cardiac output may increase the risk of maternal and fetal morbidity and mortality. Life-sustaining therapy for the pregnant woman should not be withheld due to potential concerns regarding the effects of dopamine on the fetus.

Labor or Delivery

Vasopressor drugs, including dopamine, may cause severe maternal hypertension when used concomitantly with some oxytocic drugs [see Drug Interactions (7)] .

Data

Animal Data

Animal reproduction studies in rats and rabbits at dopamine HCl dosages up to 6 mg/kg/day intravenously (on a mcg/m^2basis, one third and two thirds, respectively, the human starting dosage of 2 mcg/kg/minute) during organogenesis produced no detectable teratogenic or embryotoxic effects, although maternal toxicity consisting of mortalities, decreased body weight gain, and pharmacotoxic signs were observed in rats. In a published study, administration of 10 mg/kg/day dopamine HCl (on a mcg/m^2basis, two-thirds the human starting dosage of 2 mcg/kg/minute) to pregnant rats throughout gestation or for 5 days starting on gestation day 10 or 15 resulted in decreased body weight gain, increased mortality, and slight increase in cataract formation among the offspring.

8.2 Lactation

Risk Summary

There are no data regarding the presence of dopamine in human milk, the effects of dopamine on the breastfed infant, or the effects of the drug on milk production.

8.4 Pediatric Use

Dopamine HCl infusions have been used in pediatric patients from birth through adolescence. Most reports in pediatric patients describe dosing that is similar (on a mcg/kg/minute basis) to that used in adults [see Dosage and Administration (2.2)] . Except for vasoconstrictive effects caused by inadvertent infusion of dopamine into the umbilical artery, adverse reactions unique to pediatric patients have not been identified, nor have adverse reactions identified in adults been found to be more common in pediatric patients.

8.5 Geriatric Use

Clinical studies of dopamine did not include sufficient numbers of subjects aged 65 and over to determine whether they respond differently from younger subjects. Other reported clinical experience has not identified differences in responses between the elderly and younger patients. In general, dose selection for an elderly patient should start at the low end of the dosing range, reflecting the frequency of decreased hepatic, renal or cardiac function, and of concomitant disease or other drug therapy.

10 OVERDOSAGE

Manifestations of overdosage include excessive blood pressure elevation.

In the case of accidental overdosage, reduce rate of Dopamine HCl Injection administration or temporarily discontinue the dopamine HCl until the overdosage related adverse reactions resolves. Since dopamine’s duration of action is quite short, no additional remedial measures are usually necessary. If these measures fail to resolve the overdosage related adverse reactions, consider using an alpha-adrenergic blocking agent (e.g., phentolamine).

11 DESCRIPTION

Dopamine, a sympathomimetic amine vasopressor, is the naturally occurring immediate precursor of norepinephrine. Dopamine hydrochloride is a white to off-white crystalline powder, which may have a slight odor of hydrochloric acid. It is freely soluble in water and soluble in alcohol. Dopamine HCl is sensitive to alkalies, iron salts, and oxidizing agents. Chemically it is designated as 4-(2-aminoethyl) pyrocatechol hydrochloride, and its molecular formula is C8H11NO2• HCl. Dopamine HCl has a molecular weight of 189.64 and it has the following structural formula:

Dopamine (also referred to as 3 hydroxytyramine) is a naturally occurring endogenous catecholamine.

Dopamine hydrochloride injection is a clear, practically colorless, sterile, pyrogen-free, aqueous solution of dopamine HCl for intravenous infusion after dilution. Each milliliter of the 40 mg/mL preparation contains 40 mg of dopamine hydrochloride (equivalent to 32.31 mg of dopamine base). Each milliliter of preparation contains the following: Sodium metabisulfite 9 mg added as an antioxidant; citric acid, anhydrous 10 mg; and sodium citrate, dihydrate 5 mg added as a buffer. May contain additional citric acid and/or sodium citrate for pH adjustment. pH is 3.3 (2.5 to 5.0).

Dopamine must be diluted in an appropriate sterile parenteral solution before intravenous administration [see Dosage and Administration (2.1)] .

12 CLINICAL PHARMACOLOGY

12.1 Mechanism of Action

Dopamine is a natural catecholamine formed by the decarboxylation of 3,4 dihydroxyphenylalanine (DOPA). It is a precursor to norepinephrine in noradrenergic nerves and is also a neurotransmitter in certain areas of the central nervous system, especially in the nigrostriatal tract, and in a few peripheral sympathetic nerves.

Dopamine elicits its pharmacological action by activating dopamine D1 and D2 receptors, beta 1 receptors and alpha 1 receptors. The activation of different receptors leading to its effects are dependent on dopamine dose.

12.2 Pharmacodynamics

Dopamine’s onset of action occurs within five minutes of intravenous administration and the duration of action is less than about ten minutes. Dopamine effects are dosage‑dependent.

- At <5 mcg/kg/minute, dopamine HCl activates dopamine D1 and D2 receptors in the renal, mesenteric, and coronary vasculature causing vasodilation.
- At 5 to 10 mcg/kg/minute, dopamine HCl activates beta‑1 receptors enhancing heart rate and contractility.
- At >10 mcg/kg/minute, dopamine HCl activates alpha‑1 receptors causing vasoconstriction and increased blood pressure

12.3 Pharmacokinetics

Distribution

Following intravenous administration, dopamine is widely distributed in the body but does not cross the blood‑brain barrier to a significant extent.

Elimination

The half‑life of dopamine in adults is less than 2 minutes.

Metabolism

About 75% of dopamine is metabolized by monoamine oxidase (MAO) and catechol O‑methyl transferase (COMT) in the liver, kidney, and plasma to the inactive compounds homovanillic acid (HVA) and 3,4‑dihydroxyphenylacetic acid, and about 25% is metabolized to norepinephrine in the adrenergic nerve terminals.

Excretion

About 80% of dopamine is renally excreted as inactive metabolites within 24 hours. Dopamine is stored in vesicles or diffused back into the plasma.

Specific Populations

Pediatric Patients

The reported clearance rate of dopamine in critically ill infants and pediatric patients ranged from 46 to 168 mL/kg/minute, with the higher values seen in the younger patients. The reported apparent volume of distribution in neonates was 0.6 to 4 L/kg, leading to an elimination half life of 5 to 11 minutes.

13 NONCLINICAL TOXICOLOGY

13.1 Carcinogenesis, Mutagenesis, Impairment of Fertility

Carcinogenesis

Long term animal studies have not been performed to evaluate the carcinogenic potential of dopamine.

Mutagenesis

Dopamine HCl at doses approaching maximal solubility showed no clear genotoxic potential in the Ames test. Although there was a reproducible dose‑dependent increase in the number of revertant colonies with strains TA100 and TA98, both with and without metabolic activation, the small increase was considered inconclusive evidence of mutagenicity. In the L5178Y TK+/-mouse lymphoma assay, dopamine HCl at the highest concentrations used of 750 mcg/mL without metabolic activation, and 3000 mcg/mL with activation, was toxic and associated with increases in mutant frequencies when compared to untreated and solvent controls; at the lower concentrations no increases over controls were noted.

No clear evidence of clastogenic potential was reported in the in vivomouse or male rat bone marrow micronucleus test when the animals were treated intravenously with up to 224 mg/kg and 30 mg/kg of dopamine HCl, respectively.

16 HOW SUPPLIED/STORAGE AND HANDLING

Dopamine Hydrochloride Injection, USP is a clear, practically colorless solution supplied as follows:

Unit of Sale | Total Strength/Total Volume (Concentration)
NDC 84549-820-01 Fliptop Single-dose Vial | 200 mg/5 mL (40 mg/mL)

Store at 20°C to 25°C (68°F to 77°F). [See USP Controlled Room Temperature.]

17 PATIENT COUNSELING INFORMATION

Risk of Tissue Damage

Advise the patient, family, or caregiver to report signs of extravasation urgently [see Warnings and Precautions (5.1)].